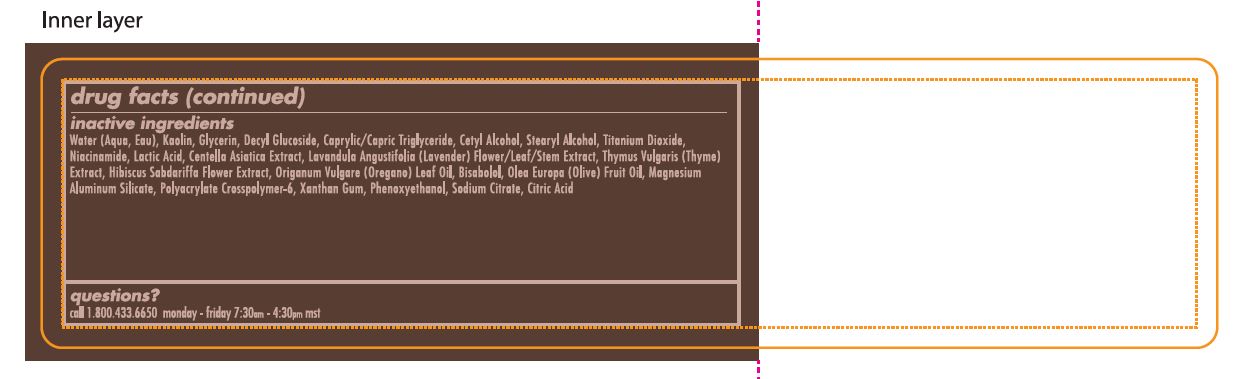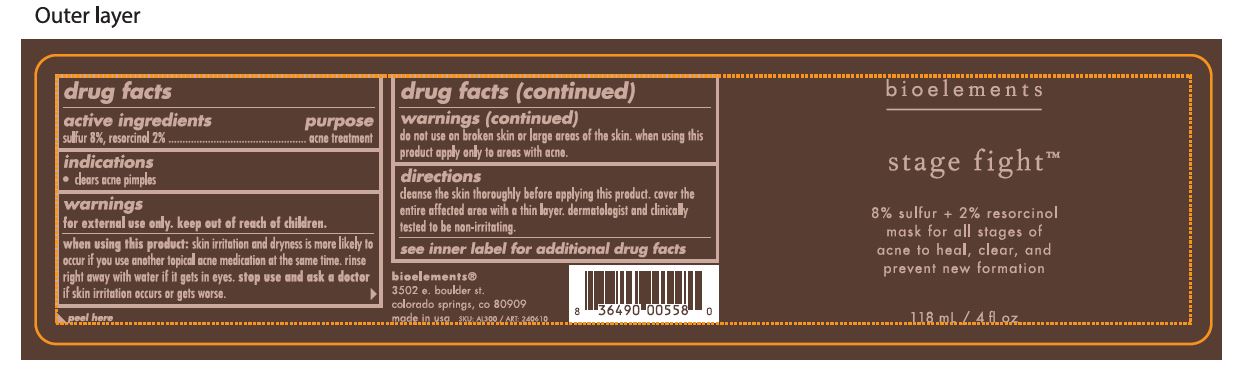 DRUG LABEL: Stage Fight Acne Mask
NDC: 49825-137 | Form: PASTE
Manufacturer: Bioelements, Inc
Category: otc | Type: HUMAN OTC DRUG LABEL
Date: 20251217

ACTIVE INGREDIENTS: SULFUR 8 g/100 mL; RESORCINOL 2 g/100 mL
INACTIVE INGREDIENTS: KAOLIN; SODIUM CITRATE; OLIVE OIL; THYME; CENTELLA ASIATICA TRITERPENOIDS; OREGANO LEAF OIL; MAGNESIUM ALUMINUM SILICATE; XANTHAN GUM; TITANIUM DIOXIDE; GLYCERIN; MEDIUM-CHAIN TRIGLYCERIDES; STEARYL ALCOHOL; LACTIC ACID; HIBISCUS SABDARIFFA FLOWER; AMMONIUM ACRYLOYLDIMETHYLTAURATE, DIMETHYLACRYLAMIDE, LAURYL METHACRYLATE AND LAURETH-4 METHACRYLATE COPOLYMER, TRIMETHYLOLPROPANE TRIACRYLATE CROSSLINKED (45000 MPA.S); PHENOXYETHANOL; CITRIC ACID MONOHYDRATE; CETYL ALCOHOL; LAVANDULA ANGUSTIFOLIA SUBSP. ANGUSTIFOLIA FLOWERING TOP; WATER; LEVOMENOL; DECYL GLUCOSIDE; NIACINAMIDE

Stage Fight Acne Mask

Active ingredients.......purpose

sulfur 8% ...................acne treatment

resorcinol 2%..............acne treatment

PURPOSE

indications

- clears acne pimples

keep out of reach of children

stop use and ask a doctor if skin irritation occurs or gets worse

Warnings

for external use only.

when using this product: skin irritation and dryness is more likely to occur if you use another topical acne medication at the same time. rinse right away with water if it gets in eyes.

do not use on broken skin or large areas of the skin. when using this product apply only to areas with acne.

directions

Cleanse the skin thoroughly before applying this product. cover the entire affected area with a thin layer. dermatologist and clinically tested to be non-irritating.

inactive ingredients

Water (Aqua, Eau), Kaolin, Glycerin, Decyl Glucoside, Caprylic/Capric Triglyceride, Cetyl Alcohol, Stearyl Alcohol, Titanium Dioxide, Niacinamide, Lactic Acid, Centella Asiatica Extract, Lavandula Angustifolia (Lavender) Flower/Leaf/Stem Extract, Thymus Vulgaris (Thyme) Extract, Hibiscus Sabdariffa Flower Extract, Origanum Vulgare (Oregano) Leaf Oil, Bisabolol, Olea Europaea (Oliva) Fruit Oil, Magnesium Aluminum Silicate, Polyacrylate Crosspolymer-6, Xantham Gum, Phenoxyethanol, Sodium Citrate, Citric Acid

PACKAGE LABEL

bioelements

stage fight

118 mL / 4 fl oz